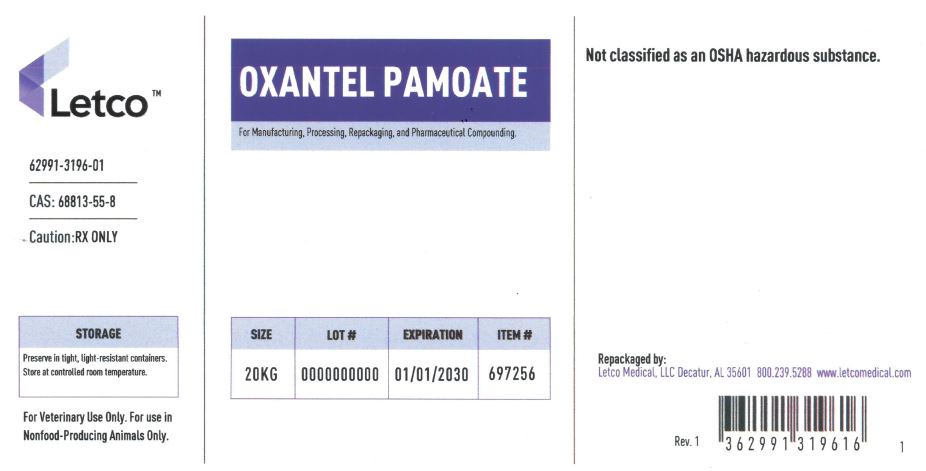 DRUG LABEL: OXANTEL PAMOATE
NDC: 62991-3196 | Form: POWDER
Manufacturer: LETCO MEDICAL, LLC
Category: other | Type: BULK INGREDIENT - ANIMAL DRUG
Date: 20240718

ACTIVE INGREDIENTS: OXANTEL PAMOATE 1 g/1 g

Oxantel Pamoate

PACKAGE LABEL

Oxantel Pamoate